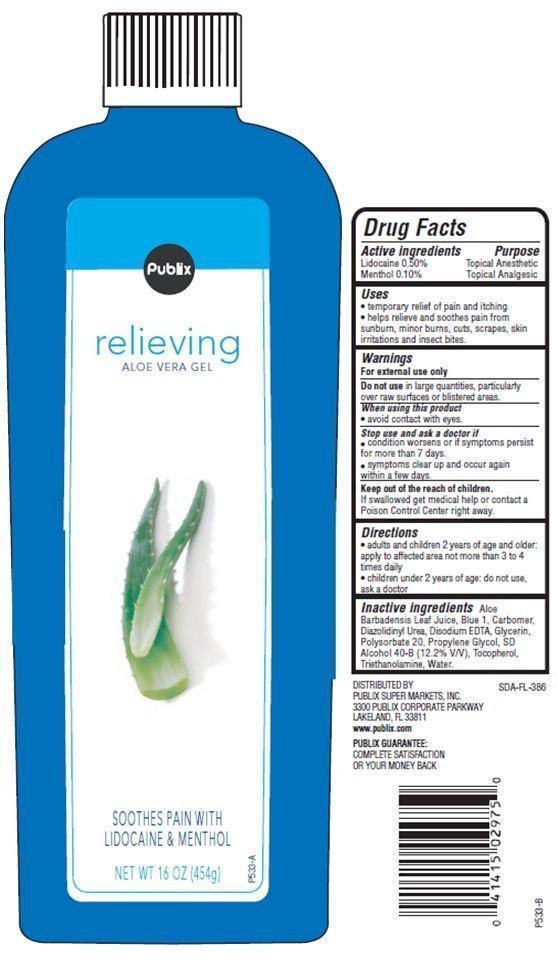 DRUG LABEL: Publix Burn Relief 
NDC: 56062-702 | Form: GEL
Manufacturer: Publix Super Markets Inc
Category: otc | Type: HUMAN OTC DRUG LABEL
Date: 20121115

ACTIVE INGREDIENTS: LIDOCAINE 0.5 g/100 g; MENTHOL 0.1 g/100 g
INACTIVE INGREDIENTS: ALOE VERA LEAF; FD&C BLUE NO. 1; DIAZOLIDINYL UREA; EDETATE DISODIUM; GLYCERIN; POLYSORBATE 20; PROPYLENE GLYCOL; TOCOPHEROL; TROLAMINE; WATER

Drug Facts

Active ingredients

Lidocaine 0.50%
Menthol 0.10%

PURPOSE

Topical Anesthetic

Uses

- temporary relief of pain and itching
- helps relieve and soothes pain from sunburn, minor burns, cuts, scrapes, skin irritations and insect bites

Warnings

For external use only

Do not use in large quantities,particularly over raw surfaces or blistered areas.

When using this product

- avoid contact with eyes.

Stop use and ask a doctor if

- condition worsens or symptoms persist for more than 7 days.
- symptoms clear up and occur again within a few days.

Keep out of reach of children.
If swallowed get medical help or contact Poison Control Center immediately.

Directions

- adults and children 2 years of age and older: apply to affected area not more than 3 to 4 times daily
- children under 2 years of age: do not use, ask a doctor

Inactive ingredients

Water, Alcohol Denat., Propylene Glycol, Glycerin, Polysorbate 20, Carbomer, Triethanolamine, Diazolidinyl Urea, Aloe Barbadensis Leaf Juice, Tocopherol, Disodium EDTA, Blue 1.

Principal Display Panel

Publix
relieving
ALOE VERA GEL
SOOTHES PAIN WITH LIDOCAINE AND MENTHOL
NET WT 16 OZ (454g)